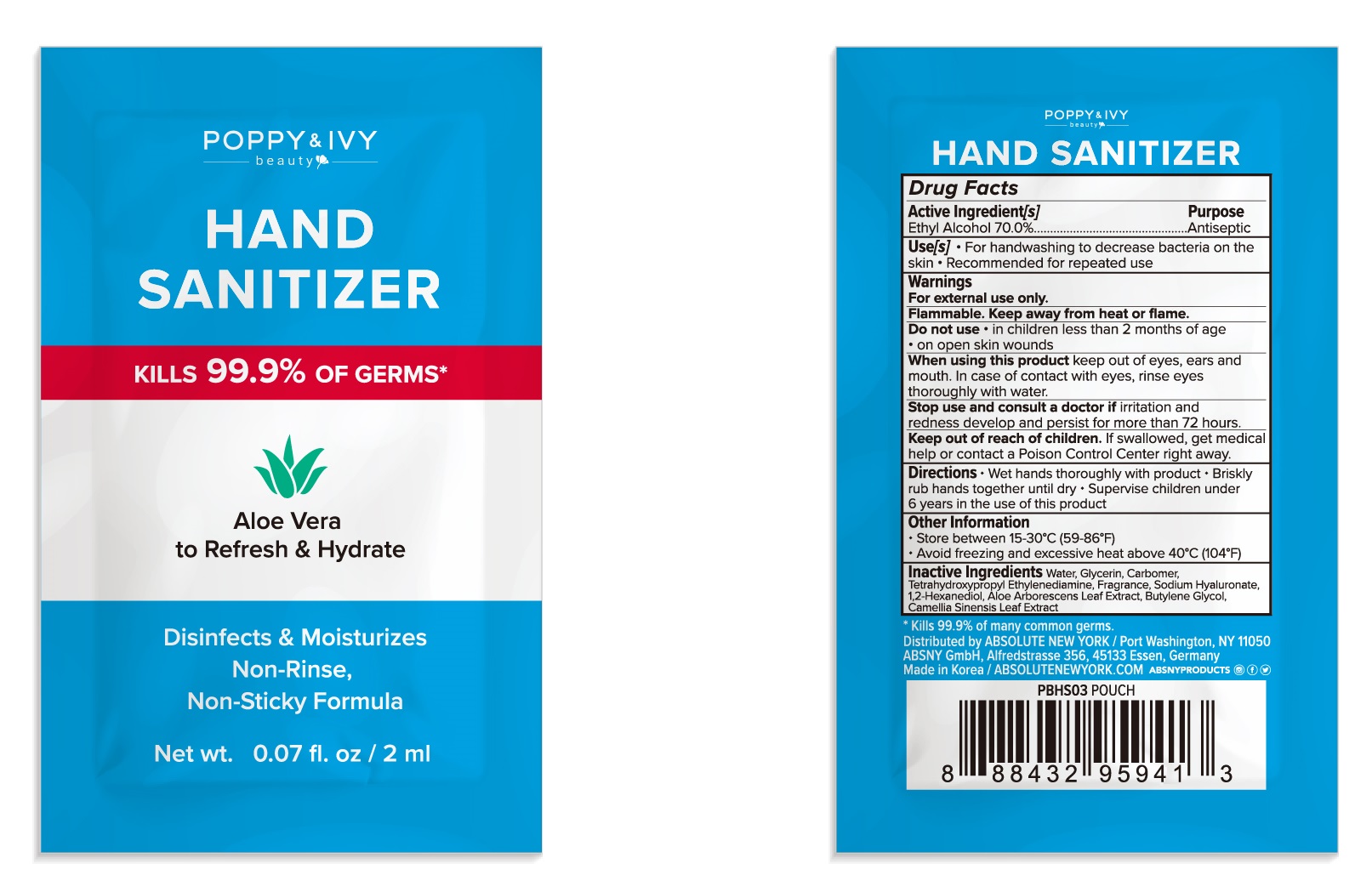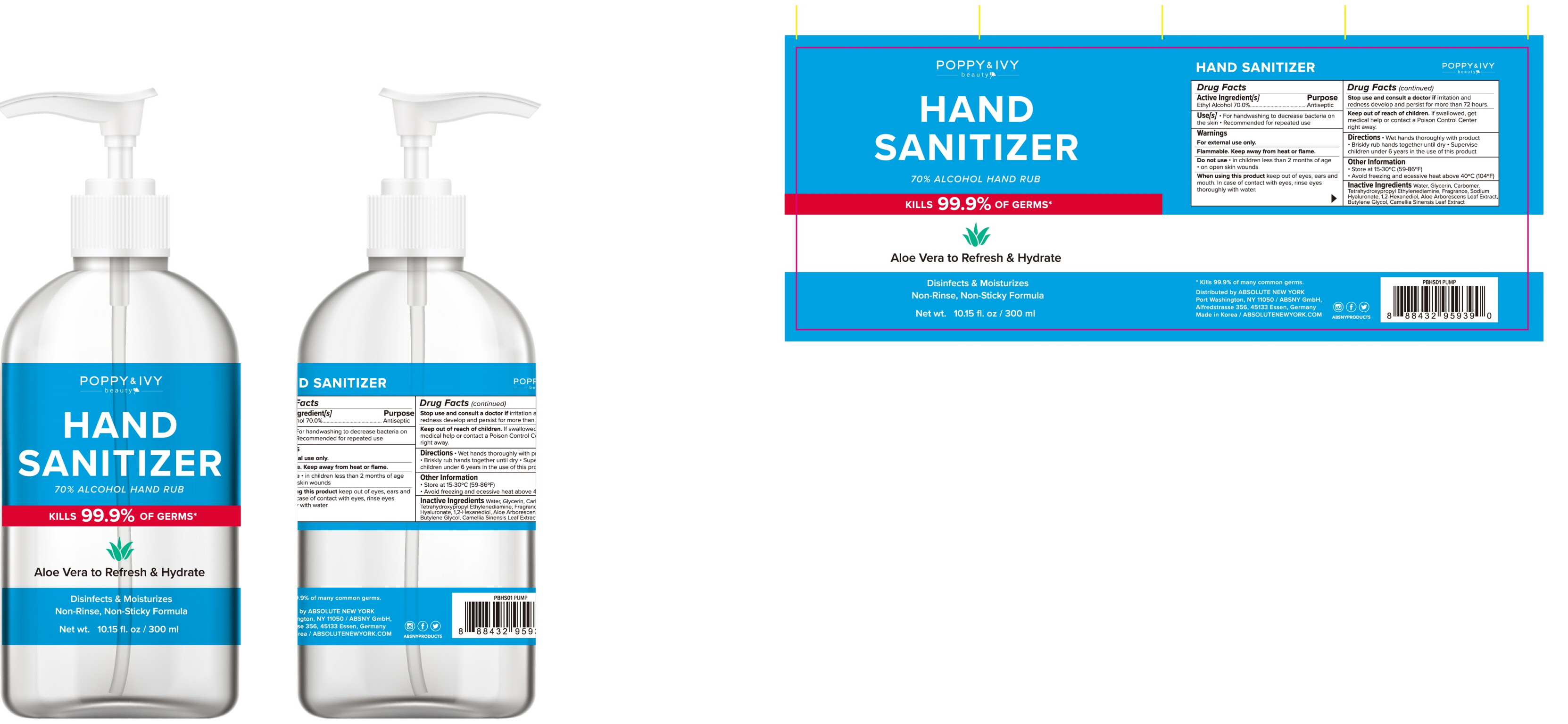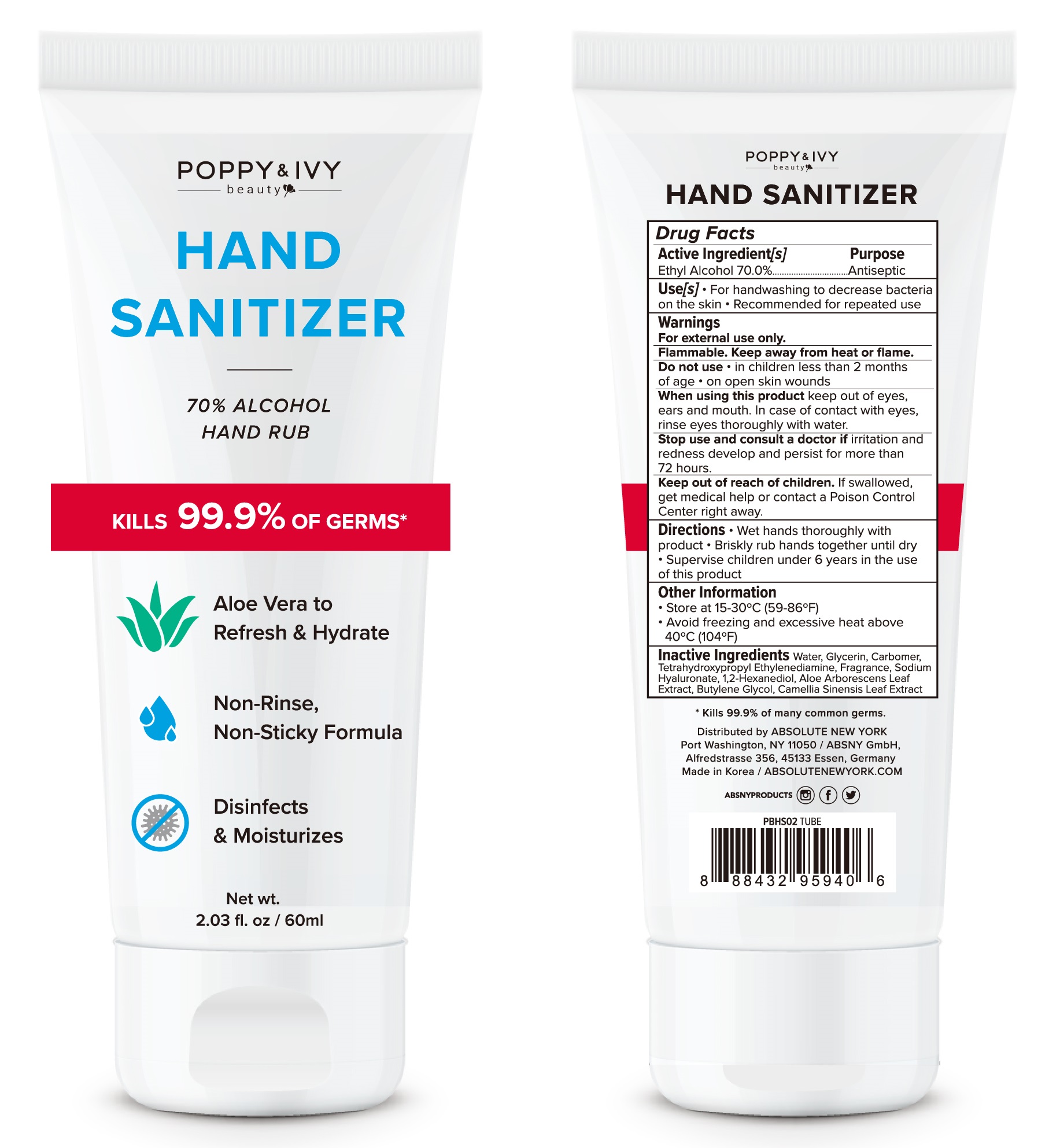 DRUG LABEL: POPPY AND IVY HAND SANITIZER
NDC: 74004-020 | Form: GEL
Manufacturer: Ester Co., Ltd.
Category: otc | Type: HUMAN OTC DRUG LABEL
Date: 20201111

ACTIVE INGREDIENTS: ALCOHOL 70 g/100 mL
INACTIVE INGREDIENTS: WATER; GLYCERIN; CARBOMER HOMOPOLYMER, UNSPECIFIED TYPE; EDETOL; HYALURONATE SODIUM; 1,2-HEXANEDIOL; ALOE ARBORESCENS LEAF; BUTYLENE GLYCOL; GREEN TEA LEAF

ACTIVE INGREDIENT

Active ingredients: ALCOHOL 70%

INACTIVE INGREDIENT

Inactive ingredients:

Water, Glycerin, Carbomer, Tetrahydroxypropyl Ethylenediamine, Fragrance, Sodium Hyaluronate, 1,2-Hexanediol, Aloe Arborescens Leaf Extract, Butylene Glycol, Camellia Sinensis Leaf Extract

PURPOSE

Purpose: ANTISEPTIC

WARNINGS

For external use only.

Flammable. Keep away from heat or flame.

Do not use • in children less than 2 months of age • on open skin wounds

When using this product keep out of eyes, ears and mouth. In case of contact with eyes, rinse eyes thoroughly with water.

Stop use and consult a doctor if irritation and redness develop and persist for more than 72 hours.

Keep out of reach of children. If swallowed, get medical help or contact a Poison Control Center right away.

KEEP OUT OF REACH OF CHILDREN

Keep our of reach of children. If swallowed get medical help or contact a Poison Control Center right away.

Uses

For handwashing to decrease bacteria on the skin

Recommended for repeated use

Directions

Wet hands thoroughly with product

Briskly rub hands together until dry

Supervise children under 6 years in the use of this product

Other Information

Store at 15-30 °C (59-86 °F)
Avoid freezing and excessive heat above 40 °C (104 °F)